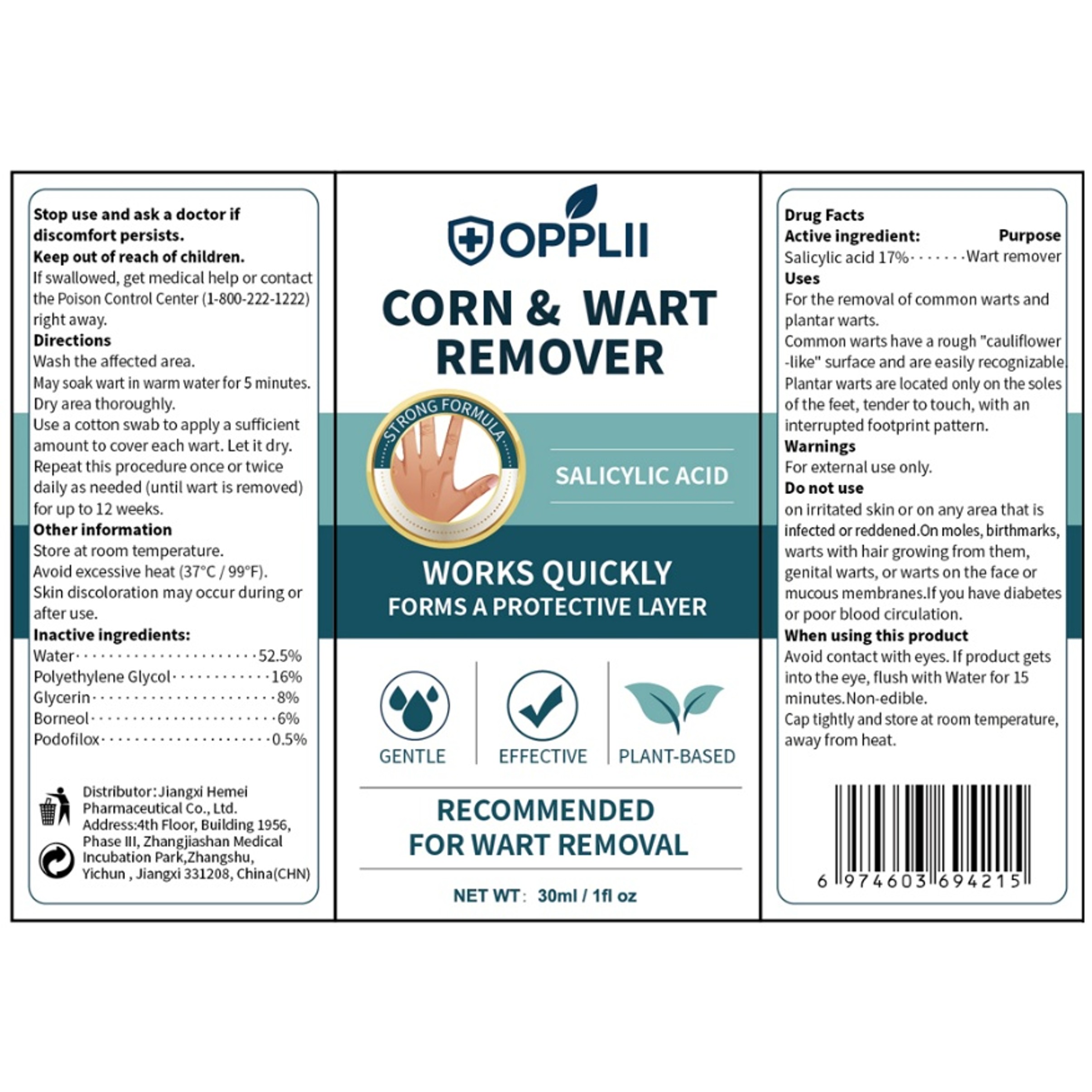 DRUG LABEL: WART REMOVER
NDC: 85825-003 | Form: LIQUID
Manufacturer: Shenzhen Haizhida E-commerce Co., Ltd
Category: otc | Type: HUMAN OTC DRUG LABEL
Date: 20250625

ACTIVE INGREDIENTS: SALICYLIC ACID 17 g/100 mL
INACTIVE INGREDIENTS: PODOFILOX; WATER; POLYETHYLENE GLYCOL, UNSPECIFIED; BORNEOL; GLYCERIN

85825-003 WART REMOVER

ACTIVE INGREDIENT

Salicylic Acid 17%

PURPOSE

Wart remover

INDICATIONS AND USAGE

For the removal of common warts andplantar warts.Common warts have a rough "cauliflower-like" surface and are easily recognizablePlantar warts are located only on the solesofthe feet, tender to touch, with aninterrupted footprint pattern.

WARNINGS

For external use only.

DO NOT USE

on irritated skin or on any area that isinfected or reddened.On moles, birthmarks.warts with hair growing from them,genital warts, or warts on the face ormucous membranes.lf you have diabetesor poor blood circulation.

WHEN USING

Avoid contact with eyes. lf product getsinto the eye, flush with Water for 15minutes.Non-edible.Cap tightly and store at room temperature,away from heat.

Stop use and ask a doctor if discomfort persists.

KEEP OUT OF REACH OF CHILDREN

If swallowed, get medical help or contactthe Poison Control Center (1-800-222-1222)right away.

DOSAGE AND ADMINISTRATION

Wash the affected area.
May soak wart in warm water for 5 minutes.
Dry area thoroughly.
Use a cotton swab to apply a sufficient amount to cover each wart. Let it dry. Repeat this procedure once or twice daily as needed (until wart is removed)for up to 12 weeks.

INACTIVE INGREDIENT

Water
Polyethylene Glycol
Borneol
Glycerin
Podofilox